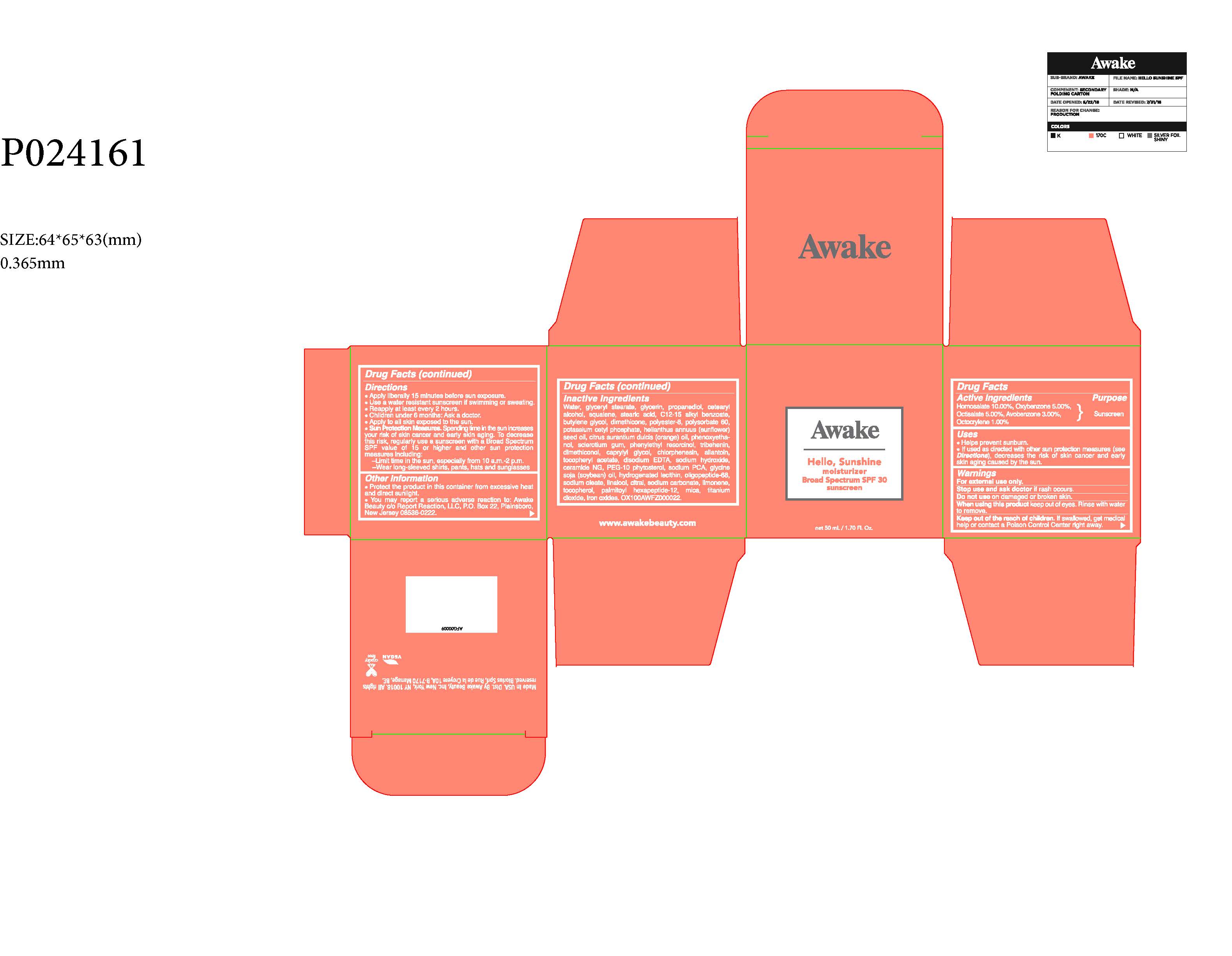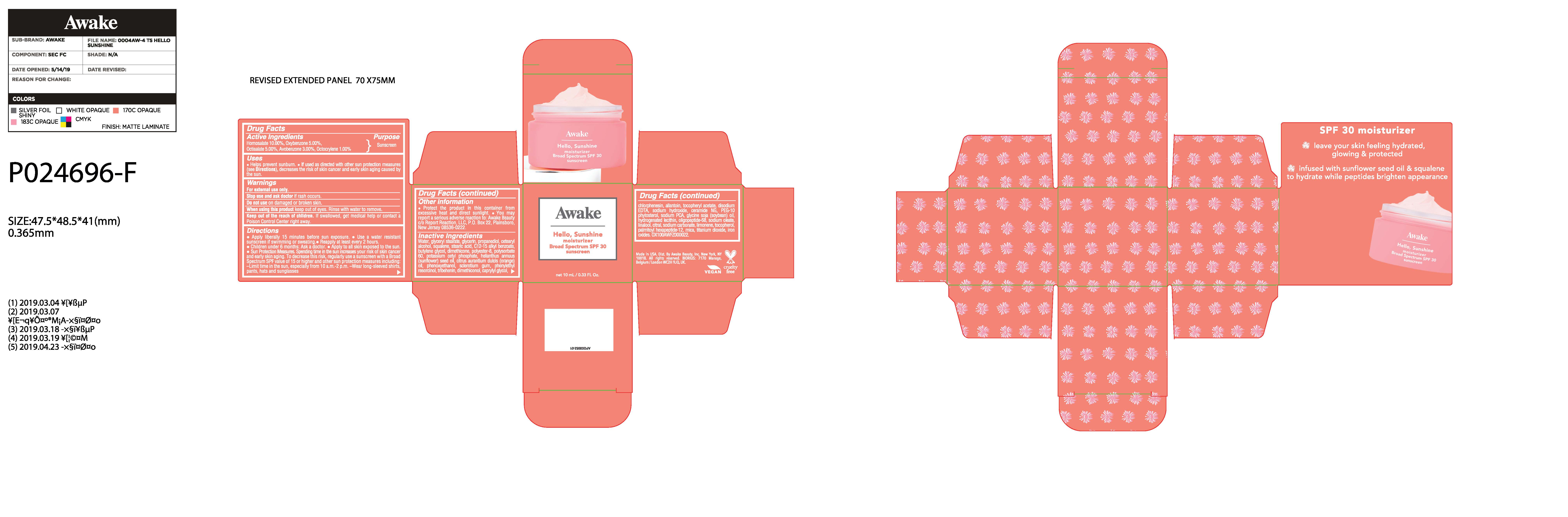 DRUG LABEL: MOISTURIZER
NDC: 61354-050 | Form: CREAM
Manufacturer: OXYGEN DEVELOPMENT, LLC
Category: otc | Type: HUMAN OTC DRUG LABEL
Date: 20210222

ACTIVE INGREDIENTS: OCTISALATE 5 mg/100 mg; AVOBENZONE 3 mg/100 mg; OXYBENZONE 5 mg/100 mg; OCTOCRYLENE 1 mg/100 mg; HOMOSALATE 10 mg/100 mg
INACTIVE INGREDIENTS: WATER; DIMETHICONE; POLYESTER-8 (1400 MW, CYANODIPHENYLPROPENOYL CAPPED); PHENOXYETHANOL; STEARIC ACID; BUTYLENE GLYCOL; SQUALANE; PHENYLETHYL RESORCINOL; GLYCERYL MONOSTEARATE; GLYCERIN; ALKYL (C12-15) BENZOATE; POTASSIUM CETYL PHOSPHATE; PROPANEDIOL; CETOSTEARYL ALCOHOL; POLYSORBATE 60; SUNFLOWER OIL; BETASIZOFIRAN

AWAKE HELLO, SUNSHINE MOISTURIZER BROAD SPECTRUM SPF 30 SUNSCREEN

Active Ingredients

Homosalate 10.00%, Oxybenzone 5.00%, Octisalate 5.00%, Avobenzone 3.00%, Octocrylene 1.00%.

Purpose

Sunscreen

Uses

- Helps prevent sunburn.
- If used as directed with other sun protection measures (see Directions), decreases the risk of skin cancer and early skin aging caused by the sun.

Warnings

For external use only.

Stop use

Stop use and ask doctor if rash occurs.

Do not use on damaged or broken skin.

When using this product keep out of eyes. Rinse with water to remove.

KEEP OUT OF REACH OF CHILDREN

Keep out of the reach of children. If swallowed, get medical help or contact a Poison Control Center right away.

Directions

- Apply liberally 15 minutes before sun exposure
- Use a water resistant sunscreen if swimming or sweating.
- Reapply at least every 2 hours.
- Children under 6 months:Ask a doctor.
- Apply to all skin exposed to the sun.
- Sun Protection Measures. Spending time in the sun increases your risk of skin cancer and early skin aging. To decrease this risk, regularly use a sunscreen with a Broad Spectrum SPF value of 15 or higher and other sun protection measures including:

-Limit time in the sun, especially from 10 a.m. - 2p.m.

-Wear long-sleeved shirts, pants, hats and sunglasses

Other Information

- Protect the product in this container from excessive heat and direct sunlight.
- You may report a serious adverse reaction to: Awake Beauty c/o Reprot Reaction, LLC, P.O. Box 22, Plainsboro, New Jersey 08536-0222.

Inactive Ingredients

Water, Glyceryl Stearate, Glycerin, Propanediol, Cetearyl Alcohol, Squalane, Stearic Acid,

C12-15 Alkyl Benzoate, Butylene Glycol, Dimethicone, Polyester-8, Polysorbate 60, Potassium Cetyl Phosphate, Helianthus Annuus (Sunflower) Seed Oil/Helianthus Annuus Seed Oil, Citrus Aurantium Dulcis (Orange) Oil, Phenoxyethanol, Sclerotium Gum, Phenylethyl Resorcinol, Tribehenin, Dimethiconol, Caprylyl Glycol, Chlorphenesin, Allantoin, Tocopheryl Acetate, Disodium EDTA, Sodium Hydroxide, Ceramide NG, PEG-10 Phytosterol, Sodium PCA, Glycine Soja (Soybean) Oil, Hydrogenated Lecithin, Oligopeptide-68, Sodium Oleate, Linalool, Citral, Sodium Carbonate, Limonene, Citronellol, Geraniol, Tocopherol, Palmitoyl Hexapeptide-12, Farnesol, Mica, Titanium Dioxide, Iron Oxides.

PACKAGE LABEL

50ml, 61354-050-01

PACKAGE LABEL

10ml, 61354-050-02